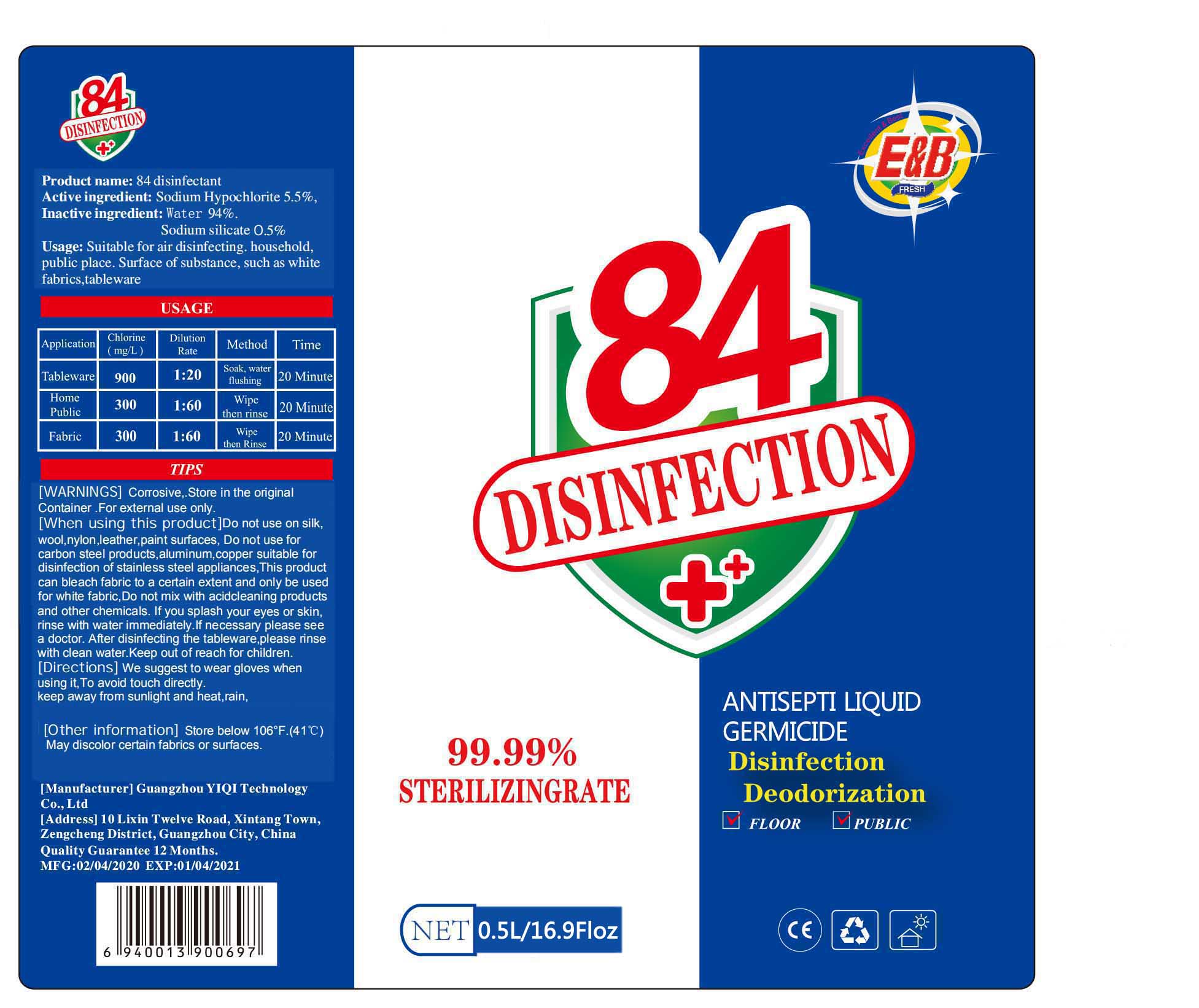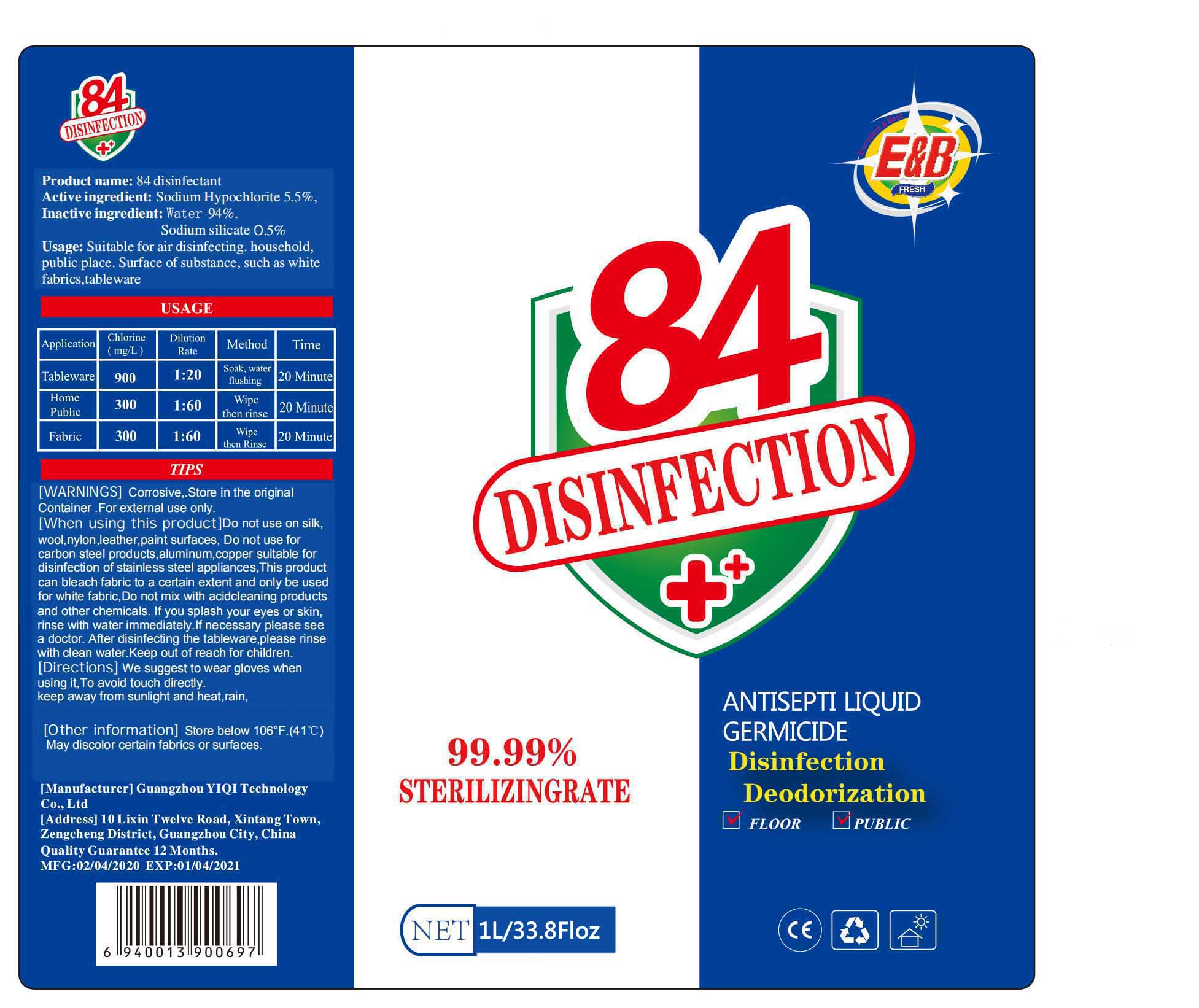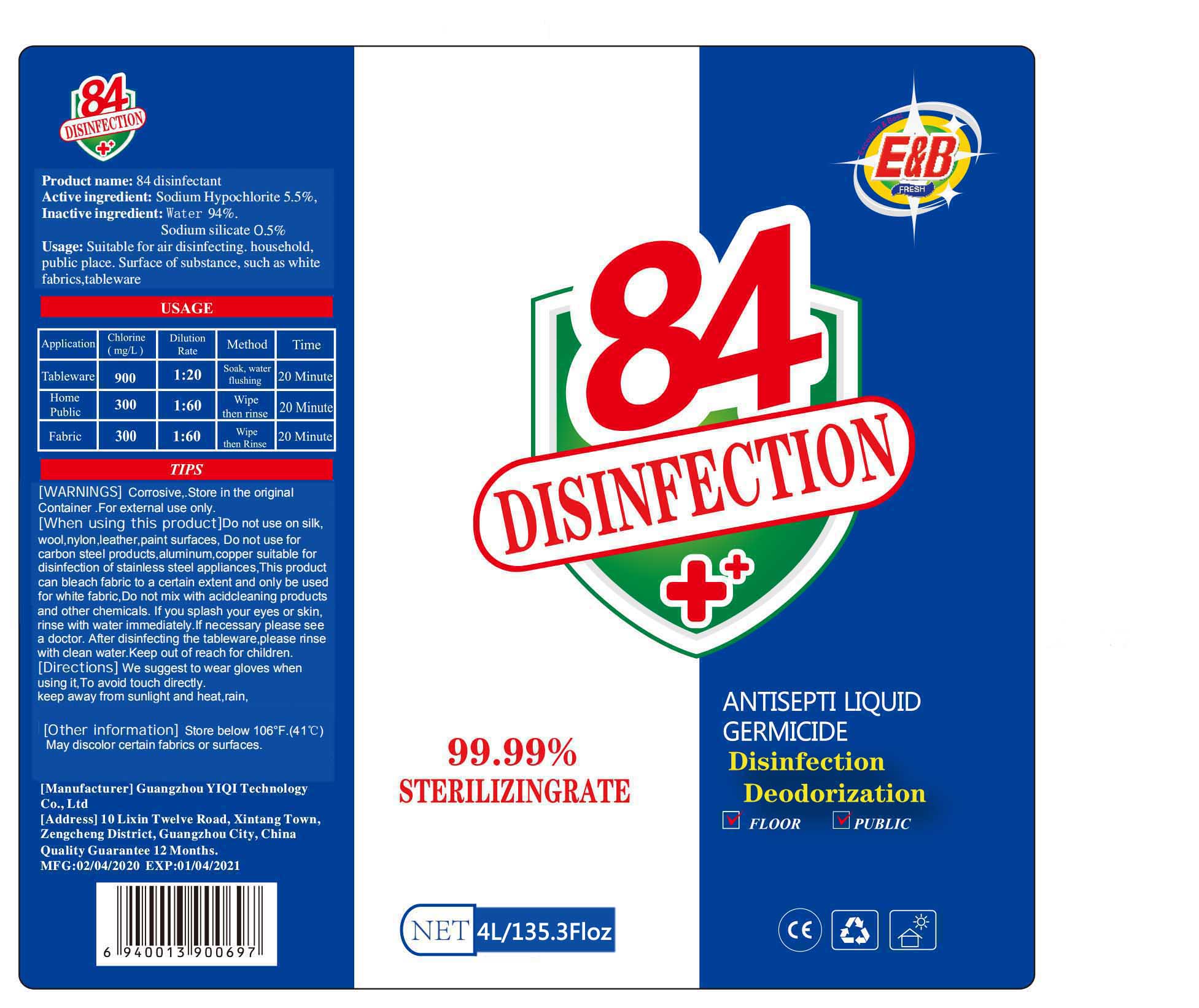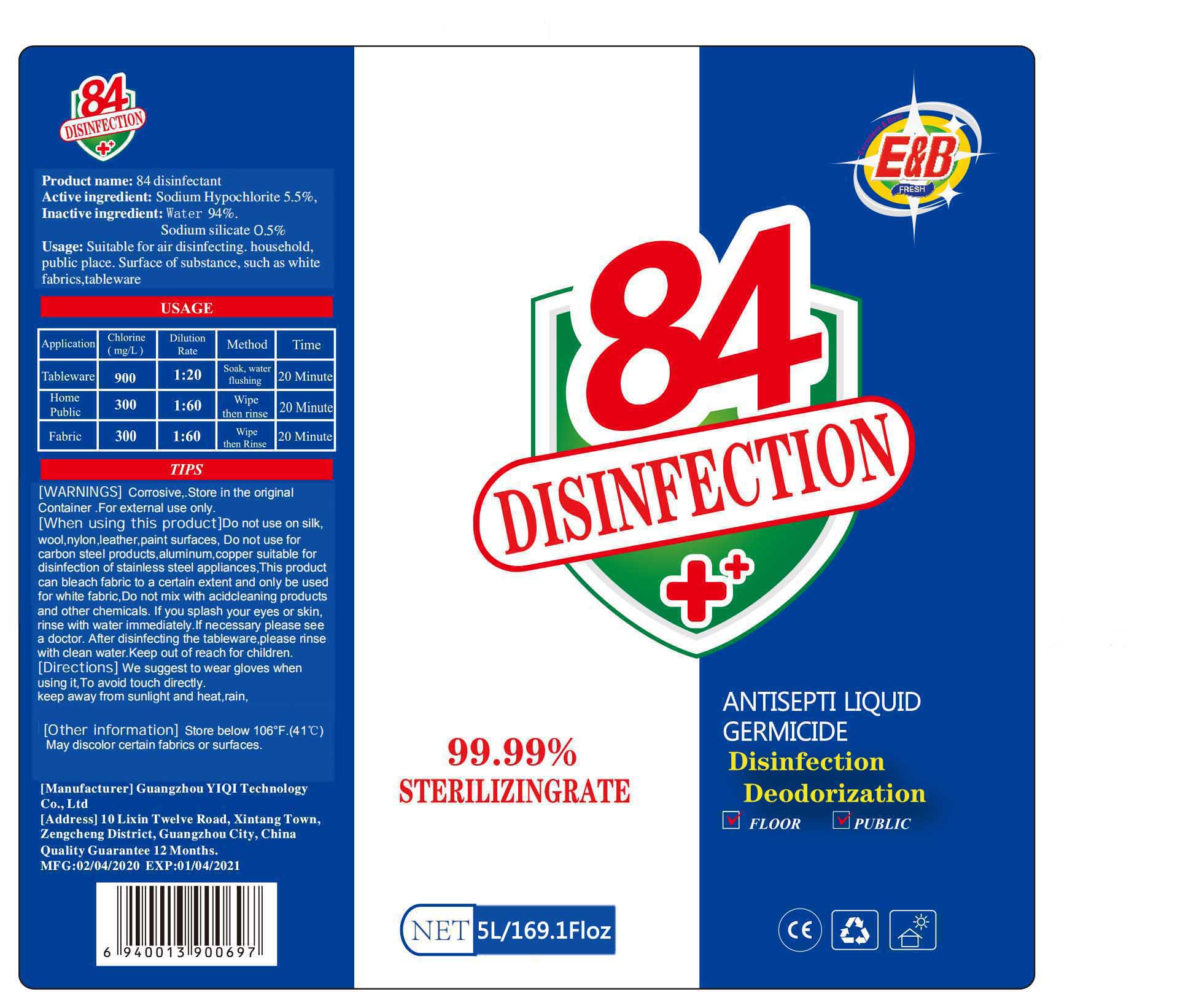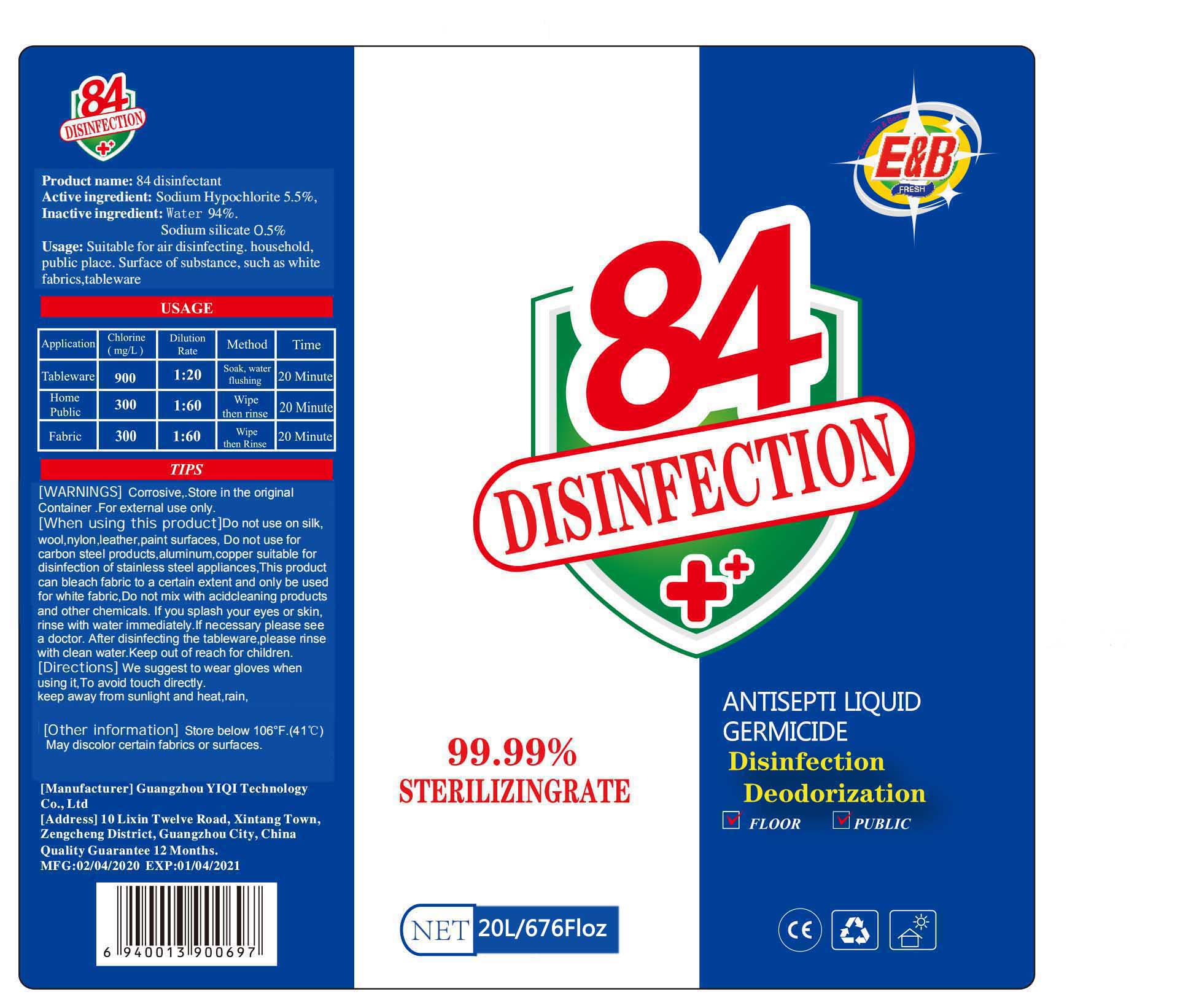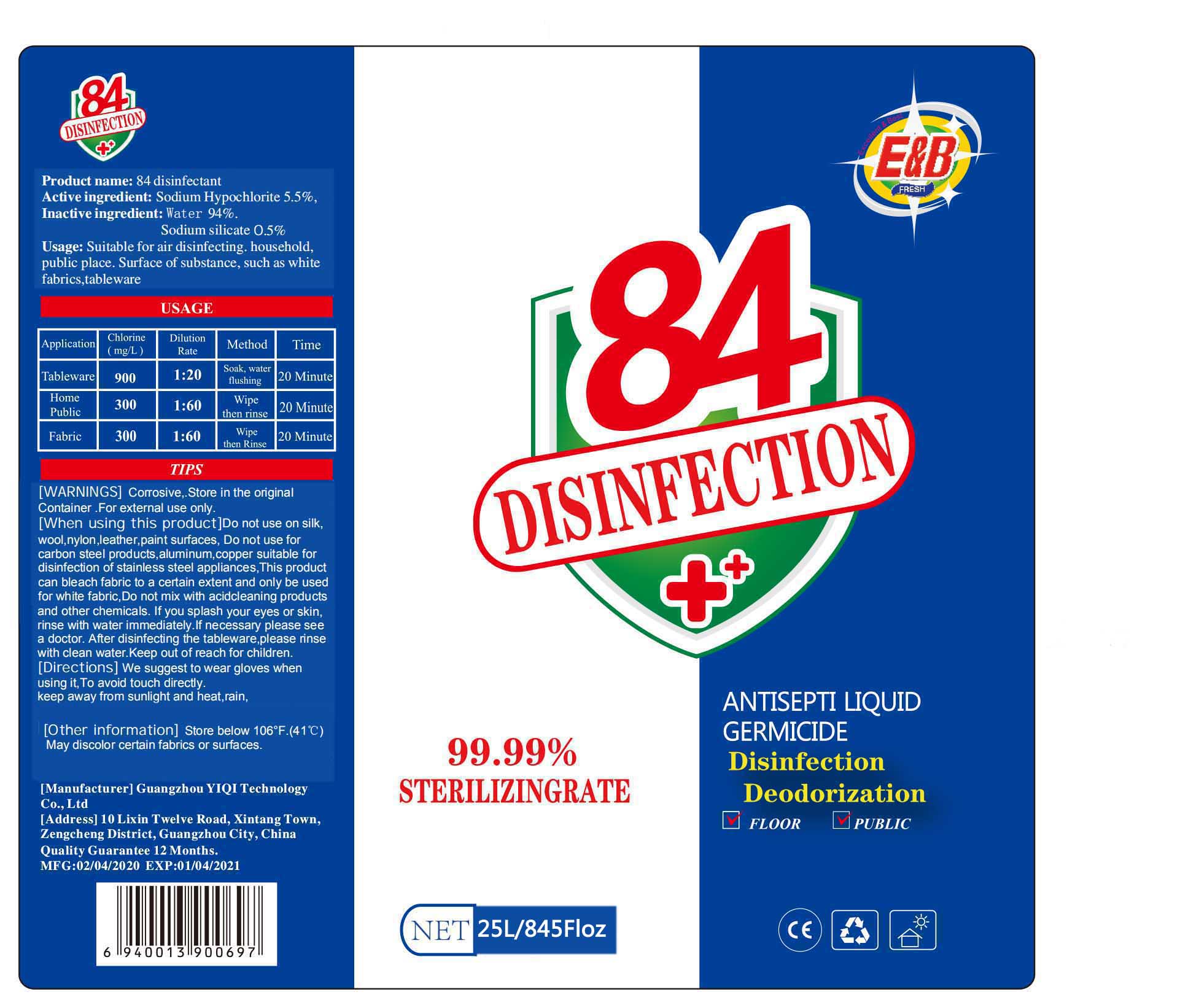 DRUG LABEL: Disinfectant
NDC: 78295-002 | Form: LIQUID
Manufacturer: GUANGZHOU YIQI TECHNOLOGY CO.,LTD
Category: otc | Type: HUMAN OTC DRUG LABEL
Date: 20200518

ACTIVE INGREDIENTS: SODIUM HYPOCHLORITE 5.5 kg/100 L
INACTIVE INGREDIENTS: SODIUM SILICATE; WATER

Disinfectant

Active ingredient

Sodium Hypochlorite 5.5%,

Usage

Suitable for air disinfecting.household,public place.Surface of substance,such as white fabrics,tableware

WARNINGS

Corrosive,Store in the original Container.For external use only.

When using this product

Do not use on silk,wool,nylon, leather, paint surfaces, Do not use for carbon steel products, aluminum,copper suitable for

disinfection of stainless steel appliances,This product can bleach fabric to a certain extent and only be used for white fabric, Do not mix with acidcleaning products and other chemicals.If you splash your eyes or skin,rinse with water immediately.If necessary please see a doctor.After disinfecing the tableware,please rinse with clean water.Keep out of reach for children.

Directions

We suggest to wear gloves when using it,To avoid touch directly.

keep away from sunlight and heat,rain,

Other information

Store below 106°F.(41℃)

May discolor certain fabrics or surfaces.

Inactive ingredient

Water 94%.

Sodium silicate 0.5%